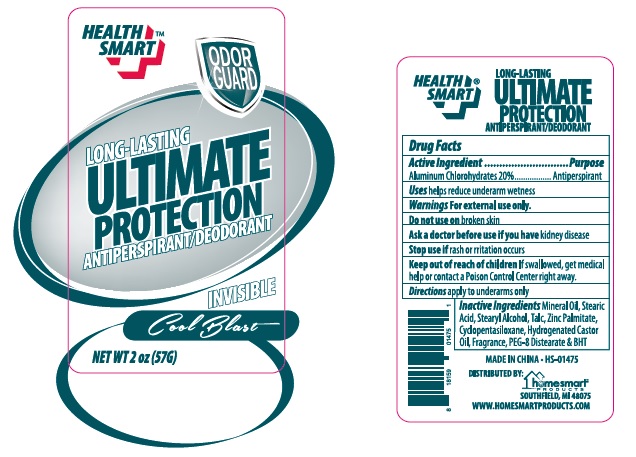 DRUG LABEL: Total Comfort Cool Blast
                        
NDC: 52862-315 | Form: STICK
Manufacturer: International Wholesale, Inc.
Category: otc | Type: HUMAN OTC DRUG LABEL
Date: 20140928

ACTIVE INGREDIENTS: ALUMINUM CHLOROHYDRATE 11.4 g/57 g
INACTIVE INGREDIENTS: MINERAL OIL; STEARIC ACID; STEARYL ALCOHOL; TALC; ZINC PALMITATE; CYCLOMETHICONE 5; CASTOR OIL; PEG-8 DISTEARATE; BUTYLATED HYDROXYTOLUENE

Total Comfort Antiperspirant & Deodorant Cool Blast

Active Ingredient

Aluminum Chlorohydrates 20%

Purpose

Antiperspirant

Uses

helps reduce underam wetness

Warnings

For external use only

Do not use on

broken skin

Ask a doctor before use

if you have kidney disease

Stop use

if rash or irritation occurs

Keep out of reach of children

If swallowed, get medical help or contact a Poison Control Center right away

Directions

apply to underams only

Inactive Ingredients

Mineral Oil, Stearic Acid, Stearyl Alcohol, Talc, Zinc Palmitate, Cyclopentasiloxane, Hydrogenated Castor Oil, Fragrance, PEG-8 Distearate,& BHT.

PACKAGE LABEL

Total Comfort

Antiperspirant & deodorant

Cool Blast

Net WT 2 oz (57 g)